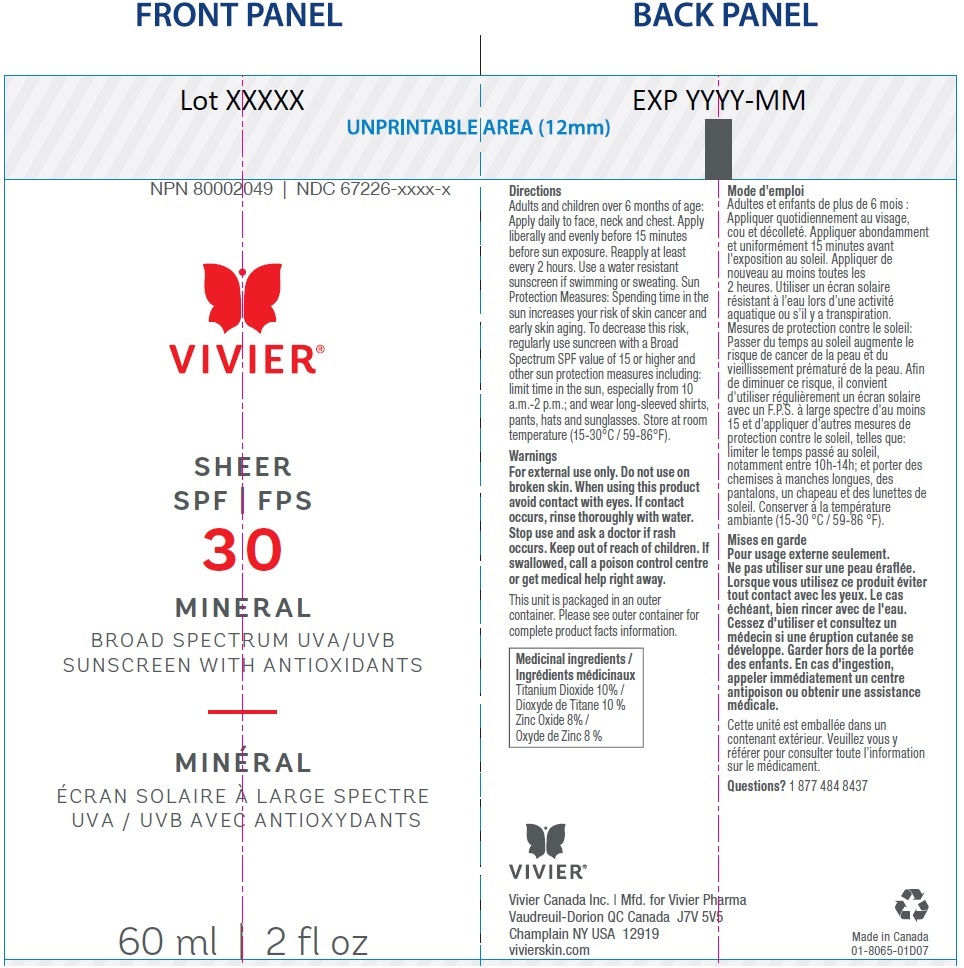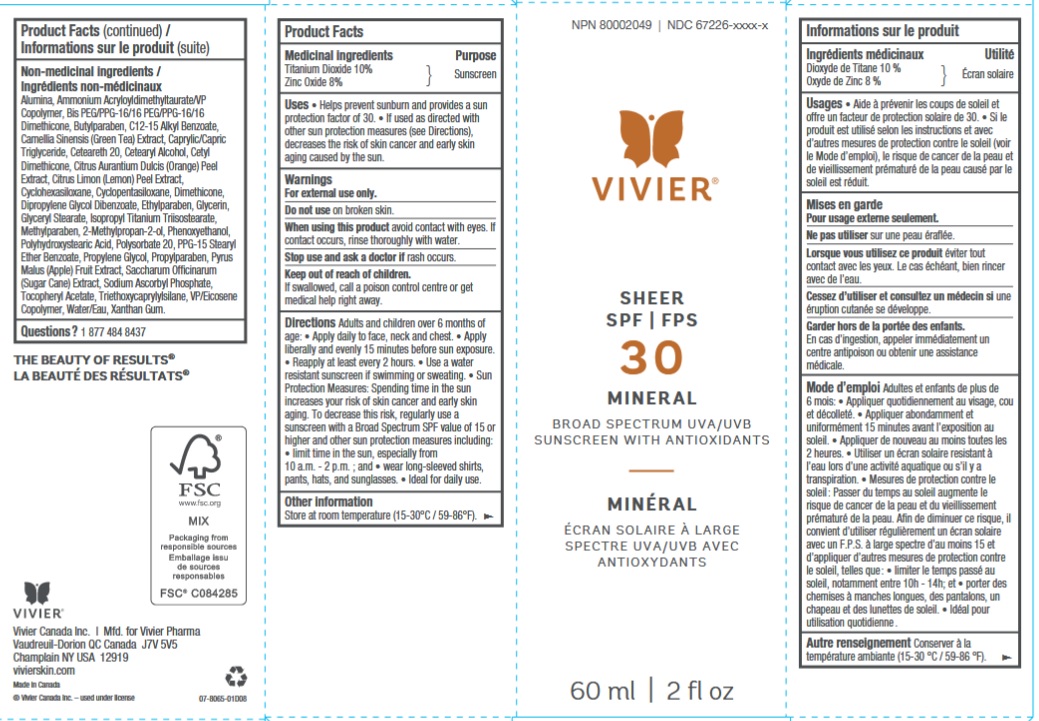 DRUG LABEL: Vivier Sheer SPF 30 Mineral
NDC: 67226-2850 | Form: LOTION
Manufacturer: Vivier Pharma, Inc.
Category: otc | Type: HUMAN OTC DRUG LABEL
Date: 20231027

ACTIVE INGREDIENTS: ZINC OXIDE 80 mg/1 mL; TITANIUM DIOXIDE 100 mg/1 mL
INACTIVE INGREDIENTS: DIMETHICONE; DIPROPYLENE GLYCOL DIBENZOATE; ETHYLPARABEN; GLYCERIN; PROPYLENE GLYCOL; PHENOXYETHANOL; ETHYL BENZOATE; POLYSORBATE 20; PROPYLPARABEN; APPLE; SUGARCANE; SODIUM ASCORBYL PHOSPHATE; TRIETHOXYCAPRYLYLSILANE; XANTHAN GUM; .ALPHA.-TOCOPHEROL ACETATE; WATER; ALUMINUM OXIDE; ISOPROPYL TITANIUM TRIISOSTEARATE; METHYLPARABEN; GLYCERYL MONOSTEARATE; AMMONIUM ACRYLOYLDIMETHYLTAURATE/VP COPOLYMER; BIS-PEG/PPG-16/16 PEG/PPG-16/16 DIMETHICONE; BUTYLPARABEN; ALKYL (C12-15) BENZOATE; GREEN TEA LEAF; MEDIUM-CHAIN TRIGLYCERIDES; POLYOXYL 20 CETOSTEARYL ETHER; CETOSTEARYL ALCOHOL; ORANGE PEEL; LEMON PEEL; CYCLOMETHICONE 6; CYCLOMETHICONE 5

Vivier Sheer SPF 30 Mineral

Active ingredients (w/w)

Octinoxate 7.5% Avobenzone 2.5%

Ensulizole 2%

Purpose

Sun Protectant

Uses

• Helps prevent sunburn • Sun Protection Factor 30 • If used as directed with other sun protection measures (see Directions), decreases the risk of skin cancer and early skin aging caused by the sun.

Warnings

For external use only.

Do not use

on broken skin.

When using this product

avoid contact with eyes. If contact occurs, rinse thoroughly with water.

Stop use and ask a doctor if

rash occurs.

Keep out of reach of children.

If swallowed, call a poison control centre or get medical help right away.

Directions

Adults and children over 6 months of age: • Apply liberally and evenly 15 minutes before sun exposure • Reapply at least every 2 hours • Sun Protection Measures: Spending time in the sun increases your risk of skin cancer and early skin aging. To decrease this risk, regularly use a sunscreen with a Broad Spectrum SPF value of 15 or higher and other sun protection measures including: • Limit time in the sun, especially from 10 a.m.– 2 p.m.; and • wear long-sleeved shirts, pants, hats, and sunglasses.

Other information

Store at room temperature (15-30°C / 59-86°F).

Inactive ingredients

Butylated Hydroxytoluene, Butylparaben, Carbomer, Cetyl Alcohol, Dimethicone, Disodium EDTA, D-Panthenol, Ethylparaben, Hydrogenated Palm Glycerides, Methylparaben, Octyldodecanol, Octyldodecyl Neopentanoate, Phenoxyethanol, Potassium Cetyl Phosphate, Propylene Glycol, Propylparaben, Sodium Hydroxide, Stearic Acid, Tocopheryl Acetate, Triethanolamine, Water.

Questions?

1 877 484 8437